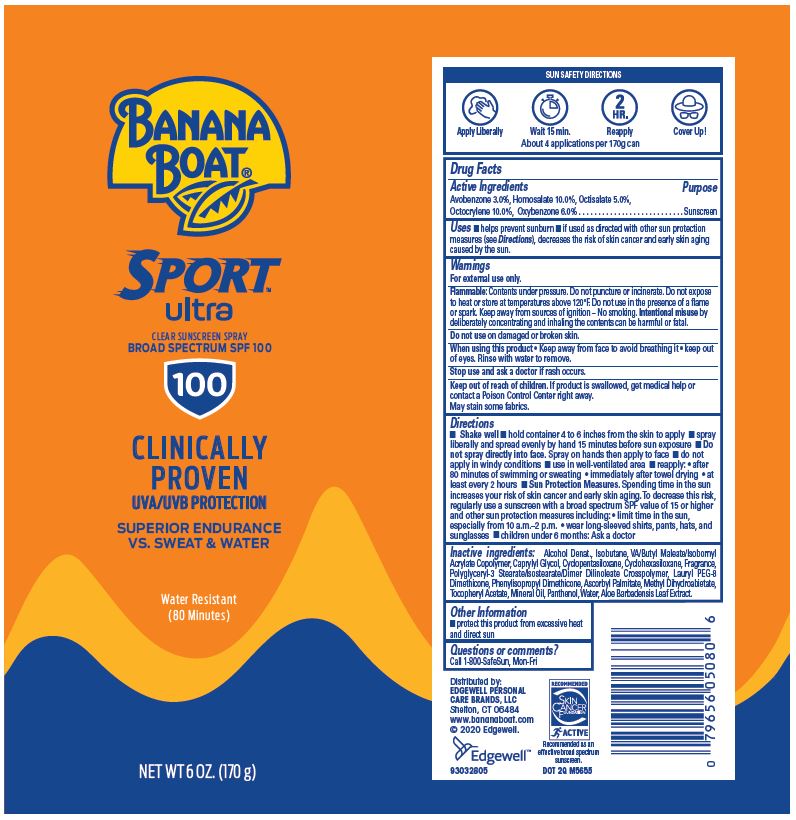 DRUG LABEL: Banana Boat
NDC: 63354-201 | Form: SPRAY
Manufacturer: Edgewell Personal Care Brands, LLC
Category: otc | Type: HUMAN OTC DRUG LABEL
Date: 20231106

ACTIVE INGREDIENTS: AVOBENZONE 3 g/100 g; OCTISALATE 5 g/100 g; OCTOCRYLENE 10 g/100 g; OXYBENZONE 6 g/100 g; HOMOSALATE 10 g/100 g
INACTIVE INGREDIENTS: ALCOHOL; ISOBUTANE; CYCLOMETHICONE 5; ASCORBYL PALMITATE; METHYL DIHYDROABIETATE; WATER; ALOE VERA LEAF; CAPRYLYL GLYCOL; ALPHA-TOCOPHEROL ACETATE; MINERAL OIL; PANTHENOL; CYCLOMETHICONE 6

Active Ingredients

Avobenzone 3.0%, Homosalate 10.0%, Octisalate 5.0%,Octocrylene 10.0%, Oxybenzone 6.0%

Purpose

Sunscreen

Uses

Helps prevent sunburn

If used as directed with other sun protection measures (see Directions), decreases the risk of skin cancer and early skin aging caused by the sun.

Warnings

For external use only.

Flammable: Contents under pressure. Do not puncture or incinerate. Do not expose to heat or store at temperatures above 120°F. Do not use in the presence of a flame or spark. Keep away from sources of ignition – No smoking. Intentional misuse by deliberately concentrating and inhaling the contents can be harmful or fatal.

May stain some fabrics

Do not use

on damaged or broken skin

When using this product

keep out of eyes. Keep away from face to avoid breathing it. Rinse with water to remove.

Stop use and ask a doctor

if rash occurs

Keep out of reach of children

If product is swallowed, get medical help or contact a Poison Control Center right away.

Directions

Shake well • hold container 4 to 6 inches from the skin to apply • spray liberally and spread evenly by hand 15 minutes before sun exposure • Do not spray directly into face. Spray on hands then apply to face • do not apply in windy conditions • use in well-ventilated area • reapply: • after 80 minutes of swimming or sweating • immediately after towel drying • at least every 2 hours • Sun Protection Measures. Spending time in the sun increases your risk of skin cancer and early skin aging. To decrease this risk, regularly use a sunscreen with a broad spectrum SPF value of 15 or higher and other sun protection measures including: • limit time in the sun, especially from 10 a.m.–2 p.m. • wear long-sleeved shirts, pants, hats, and sunglasses • children under 6 months: Ask a doctor

Inactive ingredients

Alcohol Denat., Isobutane, VA/Butyl Maleate/Isobornyl Acrylate Copolymer, Caprylyl Glycol, Cyclopentasiloxane, Cyclohexasiloxane, Fragrance, Polyglyceryl-3 Stearate/Isostearate/Dimer Dilinoleate Crosspolymer, Lauryl PEG-8 Dimethicone, Phenylisopropyl Dimethicone, Ascorbyl Palmitate, Methyl Dihydroabietate, Tocopheryl Acetate, Mineral Oil, Panthenol, Water, Aloe Barbadensis Leaf Extract.

Other information

Protect this product from excessive heat and direct sun

Questions or comments?

Call 1-800-SafeSun, Mon-Fri

Principal Display Panel

BANANA
BOAT®
SPORT
ultra
CLEAR SUNSCREEN SPRAY
BROAD SPECTRUM SPF 100
100
CLINICALLY
PROVEN
UVA/UVB PROTECTION
SUPERIOR ENDURANCE
VS. SWEAT & WATER
Water Resistant
(80 Minutes)
NET WT 6 OZ. (170 g)